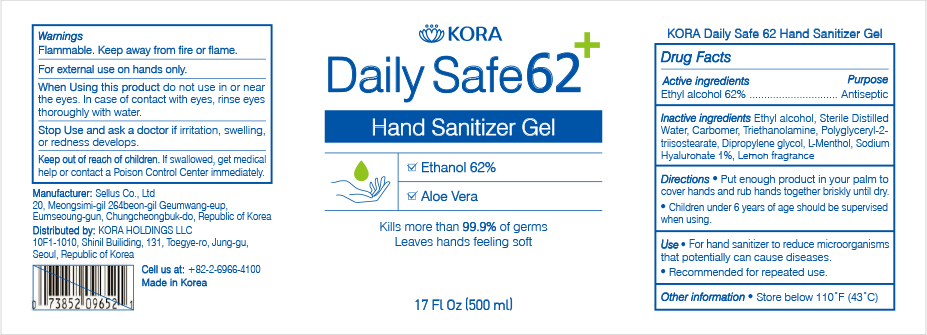 DRUG LABEL: KORA Daily Safe 62
NDC: 75504-162 | Form: GEL
Manufacturer: Kora Holdings LLC
Category: otc | Type: HUMAN OTC DRUG LABEL
Date: 20201215

ACTIVE INGREDIENTS: ALCOHOL 62 mL/100 mL
INACTIVE INGREDIENTS: CARBOMER INTERPOLYMER TYPE A (ALLYL SUCROSE CROSSLINKED) 0.3 mL/100 mL; HYALURONATE SODIUM 0.1 mL/100 mL; DIPROPYLENE GLYCOL 0.2 mL/100 mL; LEVOMENTHOL 0.1 mL/100 mL; TROLAMINE 0.4 mL/100 mL; POLYGLYCERYL-2 TRIISOSTEARATE 2 mL/100 mL; WATER 34.8 mL/100 mL; LEMON OIL 0.1 mL/100 mL

Active Ingredient(s)

Alcohol 62% v/v. Purpose: Antiseptic

Purpose

Antiseptic. Hand Sanitizer

Use

For hand sanitizer to reduct microorganisms that potentially can cause diseases. Recommended for repeated use.

Warnings

For external use on hands only. Flammable. Keep away from fire or flame.

Do not use

in or near the eyes.In case of contact with eyes, rinse eyes thoroughly with water.

When using this product do not use or near the eyes. In case of contact with eyes, rinse eyes thoroughly with water.

Stop use and ask a doctor if irritation, swelling or redness develops.

Stop use and ask a doctor if irritation, swelling or redness develops.

Keep out of reach of children. If swallowed, get medical help or contact a Poison Center immediately.

Directions

Put enough product in your palm to cover hands and rub hands together briskly until dry.

Children under 6 years of age should be supervised when using.

Other information

Store below 110°F (43°C)

Inactive ingredients

Ethyl alcohol, Sterile Distilled water, Carbomer, Triethanolamine, Polyglyceryl-2-triisostearate, Dipropylene glycol, L-Menthol, Sodium Hyaluronate 1%, Lemon fragrance

PACKAGE LABEL

500mL

NDC:75504-162-11